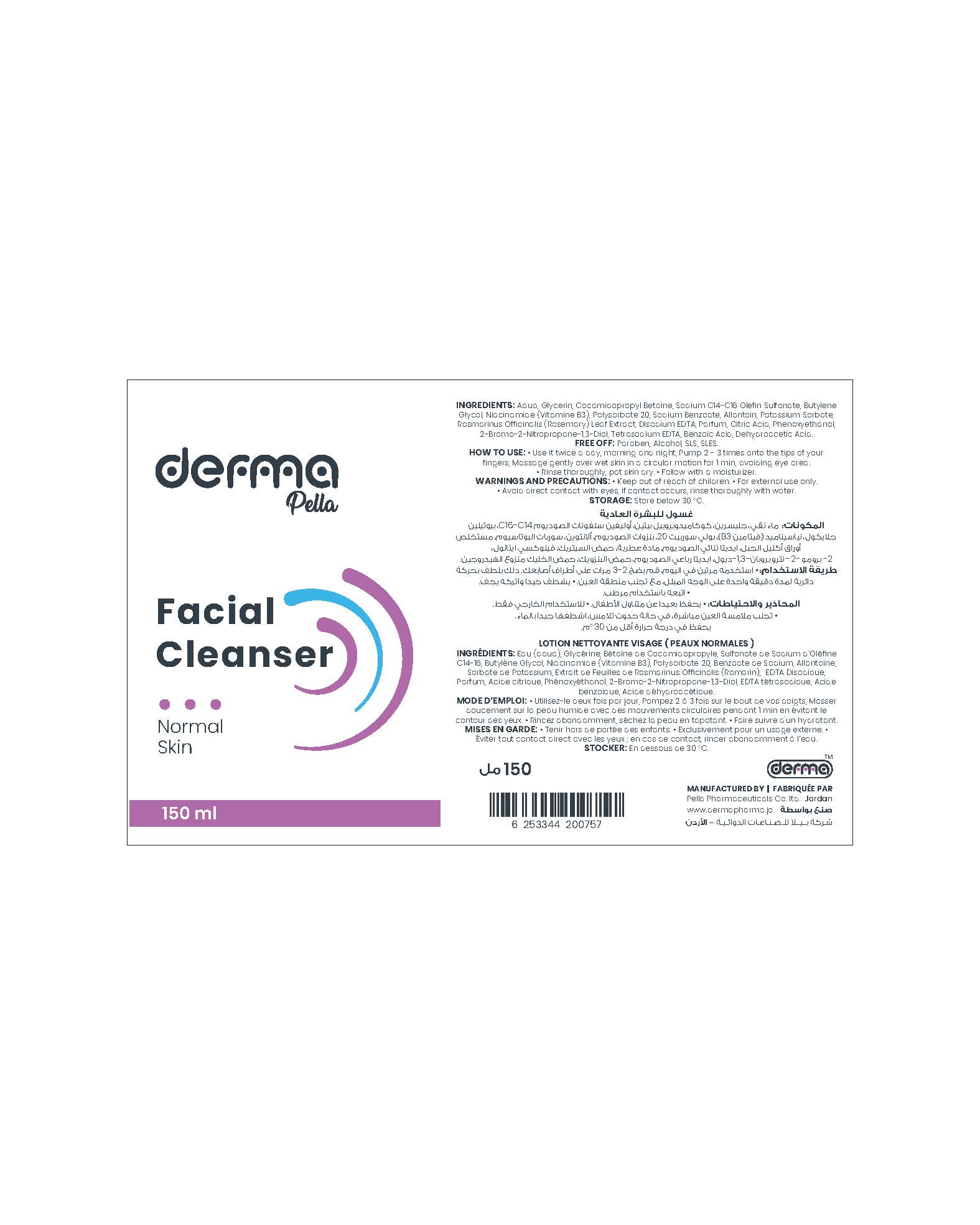 DRUG LABEL: Derma Pella Facial Cleanser for Normal Skin
NDC: 82160-757 | Form: SOLUTION
Manufacturer: Pella Pharmaceuticals Co. Ltd
Category: otc | Type: HUMAN OTC DRUG LABEL
Date: 20241231

ACTIVE INGREDIENTS: NIACINAMIDE 10 mg/1 mL
INACTIVE INGREDIENTS: EDETATE DISODIUM ANHYDROUS; SODIUM BENZOATE; ALLANTOIN; PHENOXYETHANOL; BRONOPOL; GLYCERIN; POLYSORBATE 20; BENZOIC ACID; COCAMIDOPROPYL BETAINE; POTASSIUM SORBATE; ROSEMARY; WATER; SODIUM C14-16 OLEFIN SULFONATE; BUTYLENE GLYCOL; CITRIC ACID MONOHYDRATE; EDETATE SODIUM; DEHYDROACETIC ACID

Cleanser for Normal Skin

Forms and Presentation

Solution: Plastic Bottle, 150 ml

Active Ingredients

Niacinamide (Vitamine B3)

Inactive Ingredients

Aqua, Glycerin, Cocamidopropyl Betain, Sodium C14-16 Olefin Sulfonate, Butylene Glycol, Polysorbate 20, Sodium Benzoate, Allantoin, Potassium Sorbate, Rosmarinus Officinalis (Rosemary) Leaf Extract, Disodium EDTA, Parfum, Citric Acid, Phenoxyethanol, 2-Bromo-2-Nitropropane-1,3-Diol, Tetrasodium EDTA, Benzoic Acid, Dehydroacetic Acid.

Purpose

Facial Cleanser for Normal Skin

Properties

This foaming face wash penetrates deep into your pores, scrubbing them from the inside out to eliminate dirt and oils.

Rosemary Extract makes the skin feel soft and sparkling by purifying, soothing, hydrating and provides anti-aging properties to the skin because it enriched in zinc, and vitamins A, B6, and C.

Niacinamide (Vitamin B3) helps soothe and balance the appearance of skin tone.

Allantoin which is an effective moisturizing ingredient used for it is gentle and non-irritating qualities.

Paraben free, Alcohol free, SLS free, SLES free.

Indications

A mild facial cleanser for normal skin.

Precautions

Keep out of reach of children

Warnings

- For external use only.
- Avoid direct contact with eyes, if contact occurs, rinse thoroughly with water.

Contraindications

Hypersensitivity to any of the components

Side Effects

It is well tolerated product there is no known side effect.

Dosage and Administration

- Use it twice a day, morning and evening.
- Pump 2 - 3 times onto the tips of your fingers.
- Massage gently over wet skin in a circular motion for 1 min, avoiding eye area.
- Rinse thoroughly, pat skin dry.
- Follow with a moisturizer.

Storage Conditions

Store below 30◦C